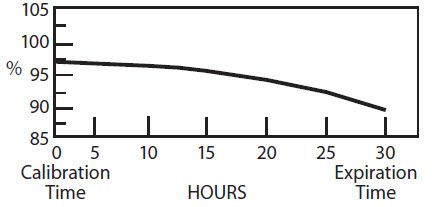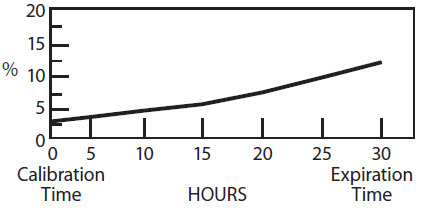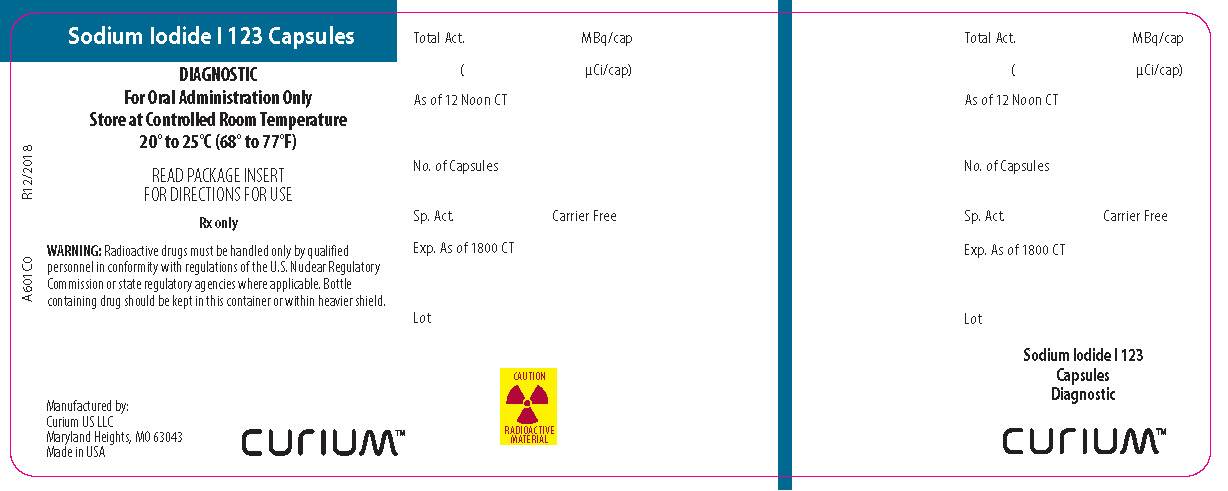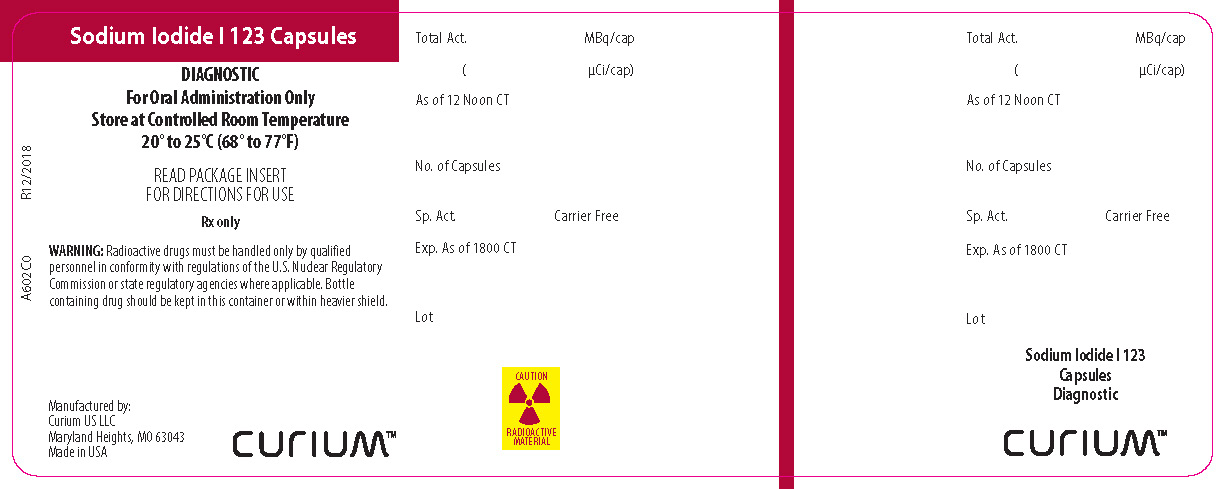 DRUG LABEL: SODIUM IODIDE I 123
NDC: 69945-601 | Form: CAPSULE, GELATIN COATED
Manufacturer: Curium US LLC
Category: prescription | Type: HUMAN PRESCRIPTION DRUG LABEL
Date: 20241017

ACTIVE INGREDIENTS: SODIUM IODIDE I-123 100 uCi/1 1
INACTIVE INGREDIENTS: SUCROSE

Sodium Iodide I 123 Capsules
Rx only
Diagnostic - For Oral Administration

DESCRIPTION

Sodium Iodide I 123 (Na^123I) for diagnostic use is supplied in capsules for oral administration. The capsules are available in strengths of 3.7 and 7.4 megabecquerels (MBq) (100 and 200 μCi) I-123 at time of calibration.

The radionuclidic composition at calibration is not less than 97.0 percent I-123, not more than 2.9 percent I-125 and not more than 0.1 percent Te-121. The radionuclidic composition at expiration time is not less than 87.2 percent I-123, not more than 12.4 percent I-125 and not more than 0.4 percent Te-121. The ratio of the concentration of I-123 and I-125 changes with time. Graph 1 shows the minimum concentration of I-123 as a function of time and Graph 2 shows the maximum concentration of I-125 as a function of time.

Graph 1. Radionuclidic Concentration of I-123

PERCENT OF TOTAL RADIOACTIVITY:
IODINE-123

Graph 2. Radionuclidic Concentration of I-125

PERCENT OF TOTAL RADIOACTIVITY:
IODINE-125

Physical Characteristics

Iodine-123 decays by electron capture with a physical half-life of 13.2 hours [Kocher, David C., Radioactive Decay Data Tables. DOE/TIC-11026, 122 (1981).] . The photon that is useful for detection and imaging studies is listed in Table 1.

Table 1. Principal Radiation Emission Data
Radiation | Mean % Disintegration | Energy (keV)
Gamma-2 | 83.4 | 159

External Radiation

The specific gamma ray constant for I-123 is 1.6 R/hr-mCi at 1 cm. The first half-value thickness of lead (Pb) for I-123 is 0.005 cm. A range of values for the relative attenuation of the radiation emitted by this radionuclide that results from the interposition of various thicknesses of Pb is shown in Table 2. For example, the use of 1.63 cm of lead will decrease the external radiation exposure by a factor of about 1,000.

Table 2. Radiation Attenuation by Lead Shielding
Shield Thickness (Pb), cm | Coefficient of Attenuation
0.005 0.10 0.88 1.63 2.48 | 0.5 10^-1 10^-2 10^-3 10^-4

Note that these estimates of attenuation do not take into consideration the presence of radionuclidic contaminants.

To correct for physical decay of I-123, the fractions that remain at selected intervals after the time of calibration are shown in Table 3.

Table 3. Iodine I-123 Decay Chart: Half-Life 13.2 Hours
Hours | Fraction Remaining |  | Hours | Fraction Remaining
0* 3 6 9 12 15 | 1.000 0.854 0.730 0.623 0.533 0.455 |  | 18 21 24 27 30 | 0.389 0.332 0.284 0.242 0.207
*Time of Calibration

CLINICAL PHARMACOLOGY

Sodium iodide I-123 is readily absorbed from the upper gastrointestinal tract. Following absorption, the iodide is distributed primarily within the extracellular fluid of the body. It is trapped and organically bound by the thyroid and concentrated by the stomach, choroid plexus and salivary glands. It is excreted by the kidneys.

The fraction of the administered dose which is accumulated in the thyroid gland may be a measure of thyroid function in the absence of unusually high or low iodine intake or administration of certain drugs which influence iodine accumulation by the thyroid gland. Accordingly, the patient should be questioned carefully regarding previous medications and/or procedures involving radiographic media. Normal subjects can accumulate approximately 10 to 50% of the administered iodine dose in the thyroid gland, however, the normal and abnormal ranges are established by individual physician's criteria. The mapping (imaging) of sodium iodide I-123 distribution in the thyroid gland may provide useful information concerning thyroid anatomy and definition of normal and/or abnormal functioning of tissue within the gland.

INDICATIONS AND USAGE

Administration of Sodium Iodide I 123 Capsules is indicated as a diagnostic procedure to be used in evaluating thyroid function and/or morphology.

CONTRAINDICATIONS

To date there are no known contraindications to the use of Sodium Iodide I 123 Capsules.

WARNINGS

Females of childbearing age and pediatric patients should not be studied unless the benefits anticipated from the performance of the test outweigh the possible risk of exposure to the amount of ionizing radiation associated with the test.

PRECAUTIONS

General

The contents of the capsule are radioactive. Adequate shielding of the preparation must be maintained at all times.

Do not use after the expiration time and date stated on the label.

The prescribed Sodium Iodide I 123 dose should be administered as soon as practical from the time of receipt of product (i.e., as close to calibration time as possible), in order to minimize the fraction of radiation exposure due to the relative increase of radionuclidic contaminants with time.

Sodium iodide I-123, as well as other radioactive drugs, must be handled with care and appropriate safety measures should be used to minimize radiation exposure to clinical personnel. Care should also be taken to minimize radiation exposure to the patient consistent with proper patient management.

Radiopharmaceuticals should be used only by physicians who are qualified by training and experience in the safe use and handling of radionuclides, and whose experience and training have been approved by the appropriate government agency authorized to license the use of radionuclides.

Carcinogenesis, Mutagenesis, Impairment of Fertility

No long-term animal studies have been performed to evaluate carcinogenic potential, mutagenic potential, or whether sodium iodide I-123 affects fertility in males or females.

Pregnancy Category C

Animal reproduction studies have not been conducted with this drug. It is also not known whether sodium iodide I-123 can cause fetal harm when administered to a pregnant woman or can affect reproductive capacity. Sodium iodide I-123 should be given to a pregnant woman only if clearly needed.

Ideally, examinations using radiopharmaceuticals, especially those elective in nature, in women of child-bearing capability should be performed during the first few (approximately ten) days following the onset of menses.

Nursing Mothers

Since I-123 is excreted in human milk, formula-feeding should be substituted for breast-feeding if the agent must be administered to the mother during lactation.

Pediatric Use

Safety and effectiveness in pediatric patients have not been established.

ADVERSE REACTIONS

Although rare, reactions associated with the administration of sodium iodide isotopes for diagnostic use include, in decreasing order of frequency, nausea, vomiting, chest pain, tachycardia, itching skin, rash and hives.

DOSAGE AND ADMINISTRATION

The recommended oral dose for the average patient (70 kg) is 3.7 to 14.8 MBq (100 to 400 μCi). The lower part of the dosage range 3.7 MBq (100 μCi) is recommended for uptake studies alone, and the higher part 14.8 MBq (400 μCi) for thyroid imaging. The determination of I-123 concentration in the thyroid gland may be initiated at six hours after administering the dose and should be measured in accordance with standardized procedures.

The patient dose should be measured by a suitable radioactivity calibration system immediately prior to administration. The capsules can be utilized up to 30 hours after calibration time and date. Thereafter, discard the capsules in accordance with standard safety procedures. The user should wear waterproof gloves at all times when handling the capsules or container.

Radiation Dosimetry

The estimated absorbed radiation doses to several organs of an average patient (70 kg) from oral administration of the maximum dose of 14.8 MBq (400 μCi) of I-123 are shown in Table 4 for thyroid uptakes of 5, 15, and 25%. For comparison at these three values of thyroid uptake, the estimated radiation doses from doses of 3.7 MBq (100 μCi) I-131, also used as thyroid imaging agent, are also included.

Table 4. Absorbed Radiation Dose Estimates as a Function of Maximum Thyroid Uptake for Sodium Iodide I-123*at Time of Calibration and Expiry Compared to Sodium Iodide I-131
 |  | Estimated Radiation Absorbed Doses
 |  | I-123 mGy/14.8 MBq (rads/400 μCi) |  | I-131 mGy/3.7 MBq (rads/100 μCi)
Target Organ | Maximum Thyroid Uptake (%) | TOC | TOE
Bladder† | 5 | 1.7 (0.17) | 1.7 (0.17) | 2.9 (0.29)
 | 15 | 1.6 (0.16) | 1.6 (0.16) | 2.7 (0.27)
 | 25 | 1.4 (0.14) | 1.5 (0.15) | 2.4 (0.24)
Stomach Wall | 5 | 0.96 (0.096) | 0.98 (0.098) | 1.7 (0.17)
 | 15 | 0.89 (0.089) | 0.91 (0.091) | 1.5 (0.15)
 | 25 | 0.82 (0.082) | 0.85 (0.085) | 1.4 (0.14)
Small Intestine | 5 | 0.70 (0.070) | 0.71 (0.071) | 1.2 (0.12)
 | 15 | 0.65 (0.065) | 0.67 (0.067) | 1.1 (0.11)
 | 25 | 0.60 (0.060) | 0.62 (0.062) | 0.99 (0.099)
Liver | 5 | 0.089 (0.0089) | 0.13 (0.013) | 0.16 (0.016)
 | 15 | 0.10 (0.010) | 0.18 (0.018) | 0.28 (0.028)
 | 25 | 0.11 (0.011) | 0.24 (0.024) | 0.41 (0.041)
Ovaries | 5 | 0.18 (0.018) | 0.19 (0.019) | 0.18 (0.018)
 | 15 | 0.17 (0.017) | 0.18 (0.018) | 0.18 (0.018)
 | 25 | 0.16 (0.016) | 0.18 (0.018) | 0.17 (0.017)
Skeleton | 5 | 0.11 (0.011) | 0.16 (0.016) | 0.12 (0.012)
 | 15 | 0.12 (0.012) | 0.18 (0.018) | 0.18 (0.018)
 | 25 | 0.14 (0.014) | 0.21 (0.021) | 0.24 (0.024)
Red Marrow | 5 | 0.12 (0.012) | 0.16 (0.016) | 0.15 (0.015)
 | 15 | 0.12 (0.012) | 0.18 (0.018) | 0.21 (0.021)
 | 25 | 0.13 (0.013) | 0.19 (0.019) | 0.27 (0.027)
Testes | 5 | 0.076 (0.0076) | 0.089 (0.0089) | 0.12 (0.012)
 | 15 | 0.072 (0.0072) | 0.087 (0.0087) | 0.12 (0.012)
 | 25 | 0.068 (0.0068) | 0.085 (0.0085) | 0.12 (0.012)
Thyroid | 5 | 25 (2.5) | 75 (7.5) | 260 (26)
 | 15 | 77 (7.7) | 230 (23) | 780 (78)
 | 25 | 130 (13) | 410 (41) | 1300 (130)
Total Body | 5 | 0.11 (0.011) | 0.16 (0.016) | 0.24 (0.024)
 | 15 | 0.14 (0.014) | 0.25 (0.025) | 0.47 (0.047)
 | 25 | 0.17 (0.017) | 0.35 (0.035) | 0.70 (0.070)
*Concentration at Time of Calibration: 97% I-123, 2.9% I-125, 0.1% Te-121
Concentration at Time of Expiry: 87.2% I-123, 12.4% I-125, 0.4% Te-121
Metabolic model in MIRD Dose Estimate Report 5 followed for I-123 and I-125
Metabolic model in ICRP 30 followed for Te-121
†Bladder voiding interval 4.8 hours.

HOW SUPPLIED

Catalog Number 601,602.

Sodium Iodide I 123 is supplied as capsules for oral administration in strengths of 3.7 MBq (100 µCi) (red and white) (NDC 69945-601-10) and 7.4 MBq (200 µCi) (green and white) (NDC 69945-602-20) at time of calibration. Each gelatin capsule contains sucrose as a filler. The capsules are packaged in plastic vials containing one capsule of a single strength per vial. The plastic vial is packaged in a lead shield. A package insert is supplied with each lead shield.

Storage and Handling

The contents of the vial are radioactive and adequate shielding and handling precautions must be maintained.

Dispense and preserve capsules in tightly-closed containers that are adequately shielded. Store at controlled room temperature 20° to 25°C (68° to 77°F).

Storage and disposal of Sodium Iodide I 123 Capsules should be controlled in a manner that is in compliance with the appropriate regulations of the government agency authorized to license the use of this radionuclide.

Curium and the Curium logo are trademarks of a Curium company.
©2018 Curium US LLC. All Rights Reserved.

Manufactured by: Curium US LLC
Maryland Heights, MO 63043

Made in USA

A601I0

R12/2018

CURIUM™

PRINCIPAL DISPLAY PANEL - A601C0

Sodium Iodide I 123 Capsules
DIAGNOSTIC
For Oral Administration Only
Store at Controlled Room Temperature
20º to 25°C (68º to 77°F)
READ PACKAGE INSERT FOR DIRECTIONS FOR USE
Rx only

WARNING:Radioactive drugs must be handled only by qualified personnel in conformity with regulations of the U.S. Nuclear Regulatory Commission or state regulatory agencies where applicable. Bottle containing drug should be kept in this container or within a heavier shield.
Manufactured by:
Curium US LLC
Maryland Heights, MO 63043
Made in USA
CURIUM™
CAUTION RADIOACTIVE MATERIAL
A601C0

R12/2018

PRINCIPAL DISPLAY PANEL - A602C0

Sodium Iodide I 123 Capsules
DIAGNOSTIC
For Oral Administration Only
Store at Controlled Room Temperature
20º to 25°C (68º to 77°F)
READ PACKAGE INSERT FOR DIRECTIONS FOR USE
Rx only
WARNING:Radioactive drugs must be handled only by qualified personnel in conformity with regulations of the U.S. Nuclear Regulatory Commission or state regulatory agencies where applicable. Bottle containing drug should be kept in this container or within a heavier shield.
Manufactured by:
Curium US LLC
Maryland Heights, MO 63043
Made in USA
CAUTION RADIOACTIVE MATERIAL

CURIUM™

A602C0 R12/2018